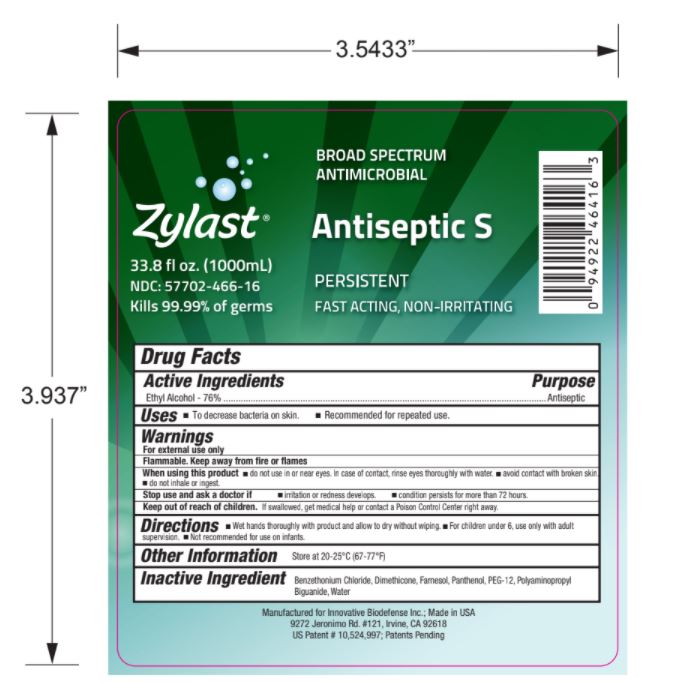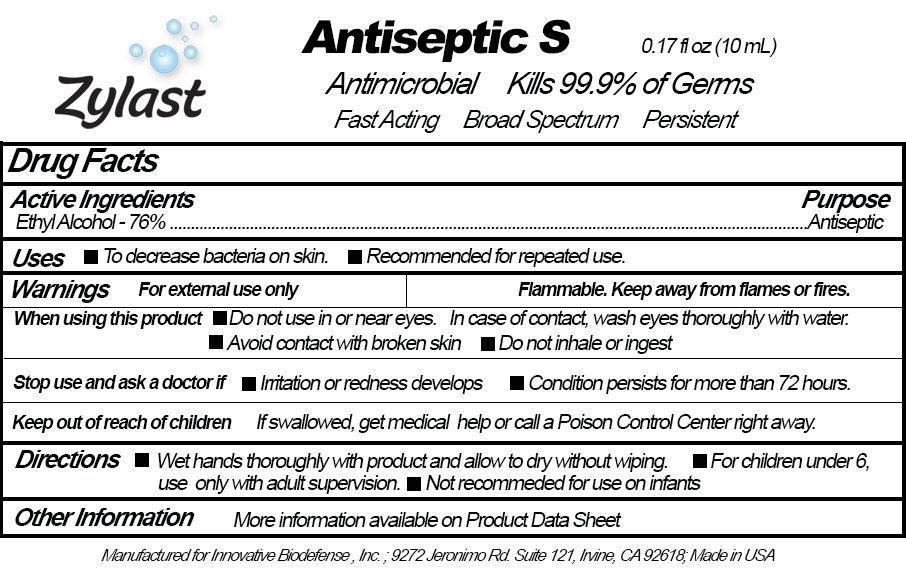 DRUG LABEL: Zylast Antiseptic S
NDC: 57362-466 | Form: LIQUID
Manufacturer: Innovative BioDefense
Category: otc | Type: HUMAN OTC DRUG LABEL
Date: 20230101

ACTIVE INGREDIENTS: ALCOHOL 760 mL/1000 mL
INACTIVE INGREDIENTS: WATER

Zylast
Antiseptic S

ACTIVE INGREDIENT

Ethyl Alcohol - 76%

PURPOSE

Antiseptic

Uses

- To decrease bacteria on skin.
- Recommended for repeated use.

Warning Section

- For external use only
- Flammable. Keep away from fire or flames.

- Do not use in or near eyes. In case of contact, rinse eyes thoroughly with water.
- Avoid contact with broken skin.
- Do not inhale or ingest.

ASK DOCTOR

Discontinue use if irritation and redness develops. Consult a doctor if condition persists for more than 72 hours.

KEEP OUT OF REACH OF CHILDREN

If swallowed, get medical help or contact a Poison Control Center right away.

Directions

- Wet hands thoroughly with product and allow to dry without wiping.
- For children under 6, use only with adult supervision.
- Not recommended for use on infants.

INACTIVE INGREDIENT

Water, Polyaminopropyl Biguanide, Panthenol, Farnesol, PEG-12, Dimethicone, Benzethonium Chloride

RECENT MAJOR CHANGES

- Inidication of Use
- Warrnings
- When using this product
- Stop use and ask a doctor
- Keep out of reach of children
- Directions
- Package Label

PACKAGE LABEL

NDC 57702-466-16

Zylast Antiseptic S

1000mL

Broad Spectrum

Antimicrobial

NDC 57362-466-10

Zylast Antiseptic S 10mL vial